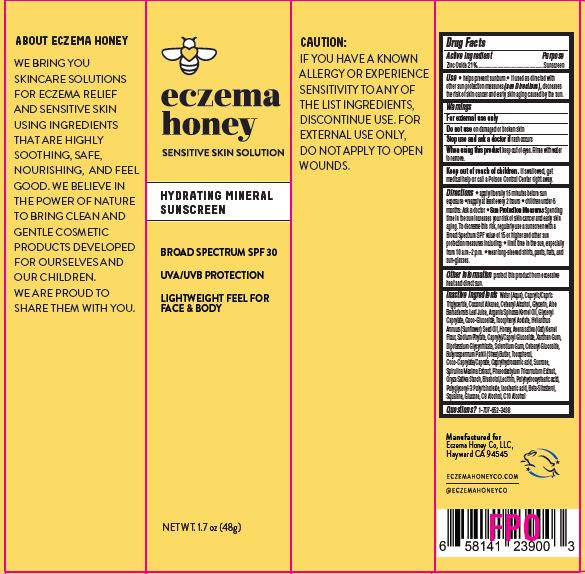 DRUG LABEL: Hydrating Mineral Sunscreen BS SPF30
NDC: 62742-4260 | Form: CREAM
Manufacturer: Allure Labs
Category: otc | Type: HUMAN OTC DRUG LABEL
Date: 20240415

ACTIVE INGREDIENTS: ZINC OXIDE 21 g/100 g
INACTIVE INGREDIENTS: HONEY; PHYTATE SODIUM; XANTHAN GUM; ISOSTEARIC ACID; SUNFLOWER OIL; SQUALENE; .BETA.-SITOSTEROL; CAPRYLHYDROXAMIC ACID; STARCH, RICE; POLYGLYCERYL-3 PENTARICINOLEATE; SPIRULINA MAXIMA; PHAEODACTYLUM TRICORNUTUM; DECYL ALCOHOL; COCO GLUCOSIDE; CETEARYL GLUCOSIDE; ALOE VERA LEAF; ARGAN OIL; OATMEAL; SHEA BUTTER; CETOSTEARYL ALCOHOL; COCONUT ALKANES; BETASIZOFIRAN; ANHYDROUS DEXTROSE; WATER; MEDIUM-CHAIN TRIGLYCERIDES; TOCOPHEROL; SUCROSE; LEVOMENOL; CAPRYLYL/CAPRYL OLIGOGLUCOSIDE; GLYCYRRHIZINATE DIPOTASSIUM; GLYCERIN; .ALPHA.-TOCOPHEROL ACETATE; GLYCERYL CAPRYLATE; COCO-CAPRYLATE/CAPRATE; LECITHIN, SOYBEAN; POLYHYDROXYSTEARIC ACID (2300 MW)

Drug Facts

Active ingredient

Zinc Oxide 21%

Purpose: Sunscreen

INDICATIONS AND USAGE

Use • helps prevent sunburn.• if used as directed with other sun protection measures (see Directions), decreases the risk of skin cancer and early skin aging caused by the sun.

Warnings For external use only

Do not use on damaged or broken skin

When using this product keep out of eyes. Rinse with water to remove.

Stop use and ask a doctor if rash occurs

Keep out of reach of children. If swallowed, get medical help or call a Poison Control Center right away.

DOSAGE AND ADMINISTRATION

Directions • apply liberally 15 minutes before sun exposure •reapply at least every 2 hours • children under 6 months: Ask a doctor • Sun Protection Measures Spending time in the sun increases your risk of skin cancer and early skin aging. To decrease this risk, regularly use a sunscreen with a Broad Spectrum SPF value of 15 or higher and other sun protection measures including: • limit time in the sun, especially from 10 a.m.-2 p.m. • wear long-sleeved shirts, pants, hats, and sun-glasses.

Other information protect this product from excessive heat and direct sun.

CAUTION:

IF YOU HAVE A KNOWN ALLERGY OR EXPERIENCE SENSITIVITY TO ANY OF THE LIST INGREDIENTS, DISCONTINUE USE. FOR EXTERNAL USE ONLY, DO NOT APPLY TO OPEN WOUNDS.

INACTIVE INGREDIENT

Inactive ingredients: Water (Aqua), Caprylic/Capric Triglyceride, Coconut Alkanes, Cetearyl Alcohol, Glycerin, Aloe Barbadensis Leaf Juice, Argania Spinosa Kernel Oil, Glyceryl Caprylate, Coco-Glucoside, Tocopheryl Acetate, Helianthus Annuus (Sunflower) Seed Oil, Honey, Avena sativa (Oat) Kernel Flour, Sodium Phytate, Caprylyl/Capryl Glucoside, Xanthan Gum, Dipotassium Glycyrrhizate, Sclerotium Gum, Cetearyl Glucoside, Butyrospermum Parkii (Shea) Butter, Tocopherol, Coco-Caprylate/Caprate, Caprylhydroxamic acid, Sucrose, Spirulina Maxima Extract, Phaeodactylum Tricornutum Extract, Oryza Sativa Starch, Bisabolol,Lecithin, Polyhydroxystearic acid, Polyglyceryl-3 Polyricinoleate, Isostearic acid, Beta-Sitosterol, Squalene, Glucose, C8 Alcohol, C10 Alcohol